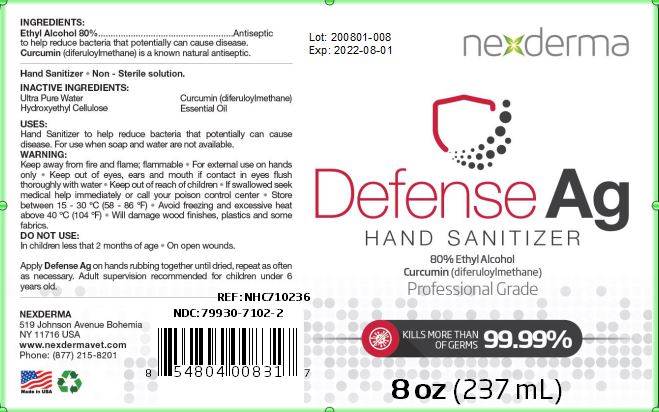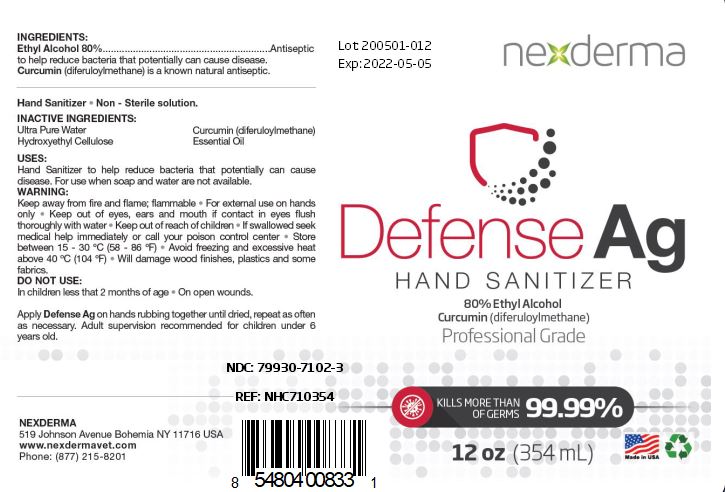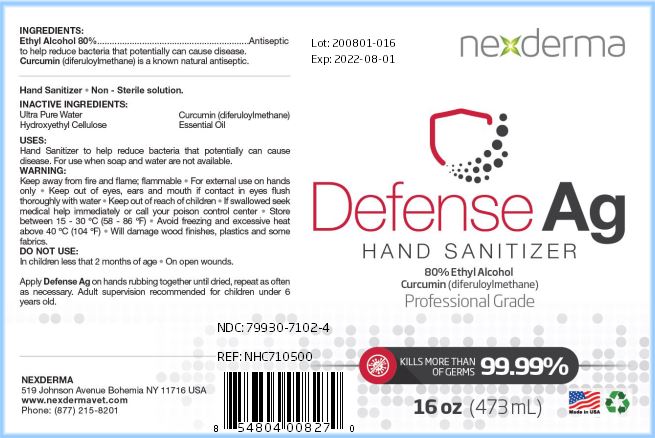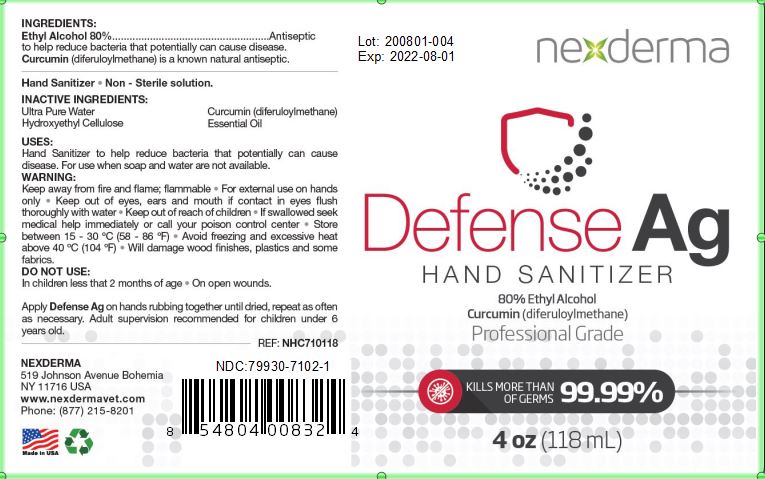 DRUG LABEL: Defense Ag
NDC: 79930-7102 | Form: GEL
Manufacturer: Nexderma Inc
Category: otc | Type: HUMAN OTC DRUG LABEL
Date: 20200930

ACTIVE INGREDIENTS: ALCOHOL 80 mL/100 mL
INACTIVE INGREDIENTS: HYDROXYETHYL CELLULOSE, UNSPECIFIED 0.2 mL/100 mL; CURCUMIN 1.3 mL/100 mL; WATER

Active Ingredient(s)

Alcohol 80% - Antiseptic to help reduce bacteria that potentially can cause disease

INACTIVE INGREDIENT

Hydroxyethyl Cellulose

Curcumin

Ultra Pure Water

Use

Hand Sanitizer to help reduce bacteria that potentially can cause disease. For use when soap and water are not available. Apply Defense Ag on hands rubbing together until dried. Repeat as often as necessary.

KEEP OUT OF REACH OF CHILDREN

Adult super vision recommended for children under 6 years old.

Warnings

Keep away from fire and flame.

Flammable

For external use on hands only

Keep out of eyes, ears and mouth.

If contact in eyes, flush thoroughly with water.

Keep out of reach of children

If swallowed seek medical help immediately or call poison control center

Store between 15-30C (58-86F)

Avoid freezing and excessive heat above 40C (104F)

Will damage wood finishes, plastics and some fabrics

Do not use

children less than 2 months of age or on open wounds.

Dosage: upto 10 times a day

Place enough product on hands to cover all surfaces. Rub hands together until dry.

Adminstration: Topical

PURPOSE

Purpose: to help reduce bacteria that potentially can cause disease. For use when soap and water are not available.

Package Label - Principal Display Panel

000 mL NDC: 00000-000-00